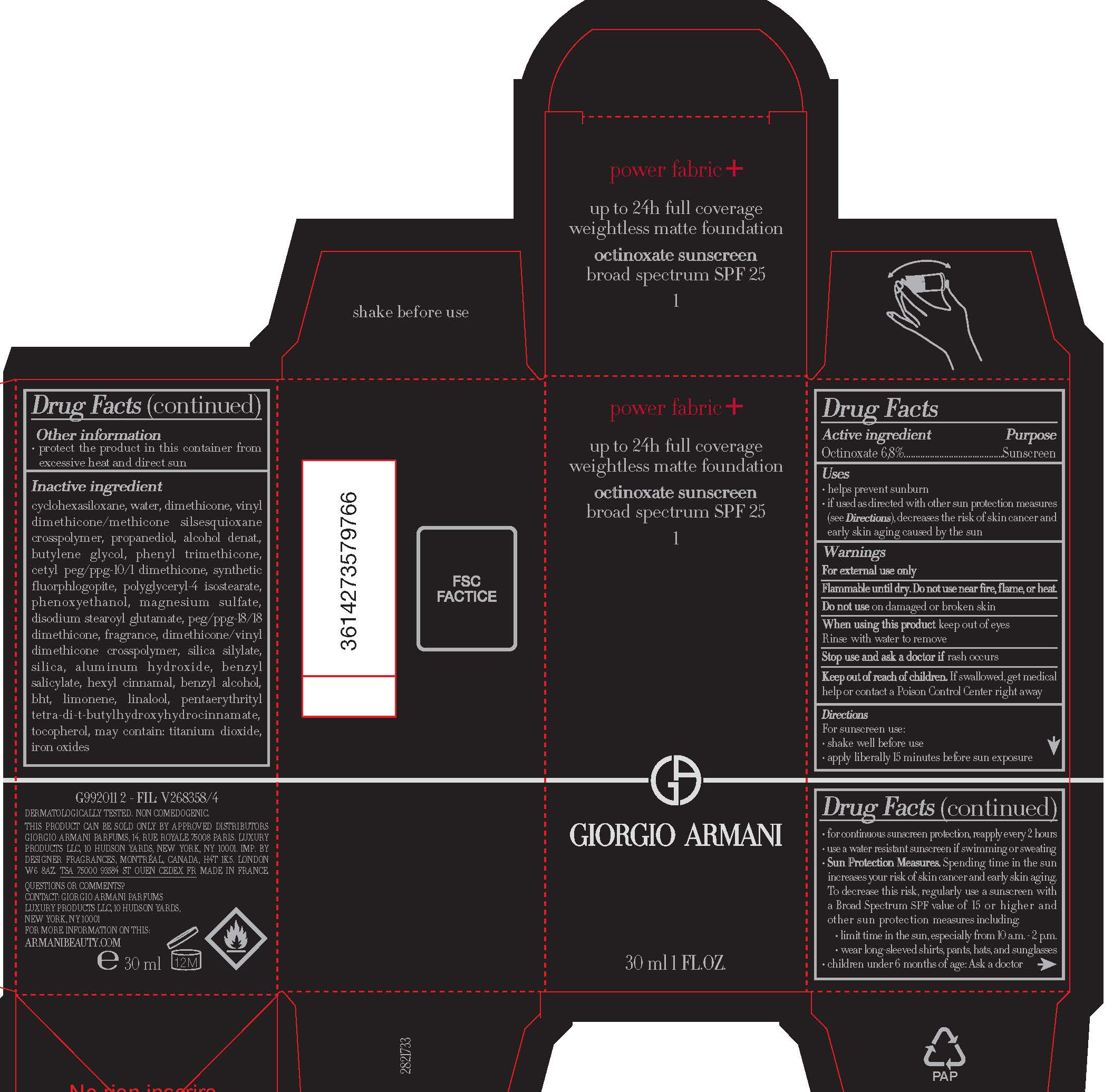 DRUG LABEL: Giorgio Armani Power Fabric Plus Weightless Matte Foundation Broad Spectrum SPF 25 Sunscreen
NDC: 49967-976 | Form: LOTION
Manufacturer: L'Oreal USA Products Inc.
Category: otc | Type: HUMAN OTC DRUG LABEL
Date: 20240624

ACTIVE INGREDIENTS: OCTINOXATE 68 mg/1 mL
INACTIVE INGREDIENTS: CYCLOMETHICONE 6; WATER; DIMETHICONE; VINYL DIMETHICONE/METHICONE SILSESQUIOXANE CROSSPOLYMER; PROPANEDIOL; ALCOHOL; BUTYLENE GLYCOL; PHENYL TRIMETHICONE; CETYL PEG/PPG-10/1 DIMETHICONE (HLB 1.5); MAGNESIUM POTASSIUM ALUMINOSILICATE FLUORIDE; POLYGLYCERYL-4 ISOSTEARATE; PHENOXYETHANOL; MAGNESIUM SULFATE, UNSPECIFIED FORM; DISODIUM STEAROYL GLUTAMATE; PEG/PPG-18/18 DIMETHICONE; DIMETHICONE/VINYL DIMETHICONE CROSSPOLYMER (HARD PARTICLE); ALUMINUM HYDROXIDE; ISOBUTANE; BENZYL SALICYLATE; .ALPHA.-HEXYLCINNAMALDEHYDE; BENZYL ALCOHOL; BUTYLATED HYDROXYTOLUENE; LIMONENE, (+)-; LINALOOL, (+/-)-; PENTAERYTHRITOL TETRAKIS(3-(3,5-DI-TERT-BUTYL-4-HYDROXYPHENYL)PROPIONATE); TOCOPHEROL; TITANIUM DIOXIDE; FERRIC OXIDE RED

Drug Facts

Active ingredient

Octinoxate 6.7%

Purpose

Sunscreen

Uses

- helps prevent sunburn
- if used as directed with other sun protection measures (see Directions), decreases the risk of skin cancer and early skin aging caused by the sun

Warnings

For external use only

Flammable until dry.

Do not use near fire, flame, or heat.

Do not use

on damaged or broken skin

When using this product

keep out of eyes. Rinse with water to remove.

Stop use and ask a doctor if

rash occurs

Keep out of reach of children.

If swallowed, get medical help or contact a Poison Control Center right away.

Directions

For sunscreen use:

● apply liberally 15 minutes before sun exposure

● reapply at least every 2 hours

● use a water resistant sunscreen if swimming or sweating

● Sun Protection Measures. Spending time in the sun increases your risk of skin cancer and early skin aging. To decrease this risk, regularly use a sunscreen with a Broad Spectrum SPF value of 15 or higher and other sun protection measures including:

● limit time in the sun, especially from 10 a.m. – 2 p.m.

● wear long-sleeved shirts, pants, hats, and sunglasses

● children under 6 months of age: Ask a doctor

Other information

protect the product in this container from excessive heat and direct sun

Inactive ingredients

cyclohexasiloxane, water, dimethicone, vinyl dimethicone/methicone silsesquioxane crosspolymer, propanediol, alcohol denat., butylene glycol, phenyl trimethicone, cetyl PEG/PPG-10/1 dimethicone, synthetic fluorphlogopite, polyglyceryl-4 isostearate, phenoxyethanol, magnesium sulfate, disodium stearoyl glutamate, acrylonitrile/methyl methacrylate/vinylidene chloride copolymer, PEG/PPG-18/18 dimethicone, fragrance, dimethicone/vinyl dimethicone crosspolymer, aluminum hydroxide, isobutene, benzyl salicylate, hexyl cinnamal, benzyl alcohol, BHT, limonene, linalool, pentaerythrityl tetra-di-t-butyl hydroxyhydrocinnamate, tocopherol, may contain: titanium dioxide, iron oxides

Questions or comments?

CONTACT: GIORGIO ARMANI PARFUMS

LUXURY PRODUCTS LLC

10 HUDSON YARDS, NEW YORK, NY 10001